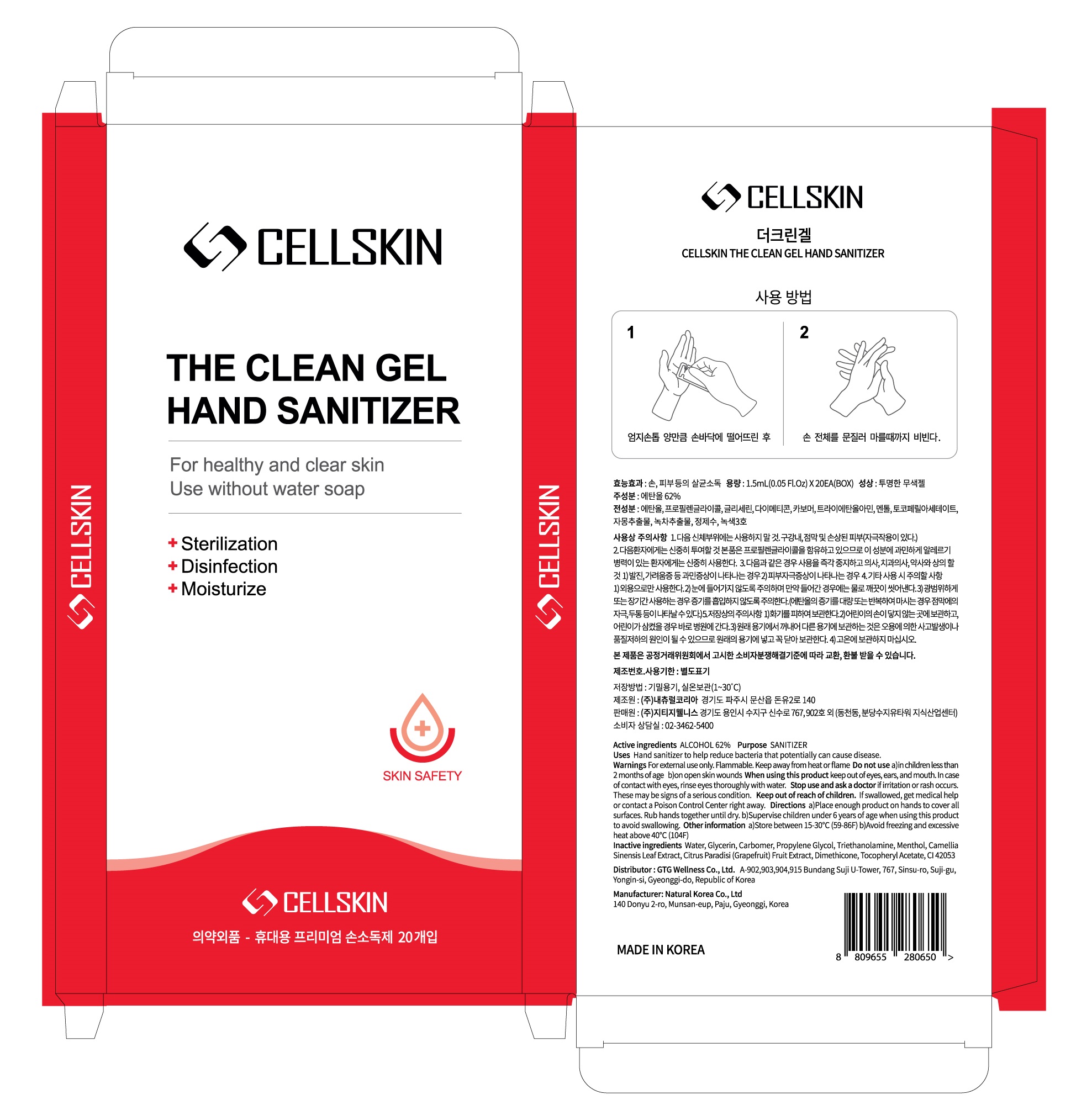 DRUG LABEL: CELLSKIN THE CLEAN HAND SANITIZER
NDC: 71080-0018 | Form: GEL
Manufacturer: GTG Wellness Co., Ltd.
Category: otc | Type: HUMAN OTC DRUG LABEL
Date: 20200601

ACTIVE INGREDIENTS: ALCOHOL 0.93 g/1.5 mL
INACTIVE INGREDIENTS: Water; Glycerin; CARBOMER HOMOPOLYMER, UNSPECIFIED TYPE; Propylene Glycol; TROLAMINE; Menthol; GREEN TEA LEAF; GRAPEFRUIT; Dimethicone; .ALPHA.-TOCOPHEROL ACETATE

ACTIVE INGREDIENT

ALCOHOL 62%

INACTIVE INGREDIENTS

Water, Glycerin, Carbomer, Propylene Glycol, Triethanolamine, Menthol, Camellia Sinensis Leaf Extract, Citrus Paradisi (Grapefruit) Fruit Extract,
Dimethicone, Tocopheryl Acetate, CI 42053

PURPOSE

SANITIZER

WARNINGS

For external use only. Flammable. Keep away from heat or flame
--------------------------------------------------------------------------------------------------------
Do not use
• in children less than 2 months of age
• on open skin wounds
--------------------------------------------------------------------------------------------------------
When using this product keep out of eyes, ears, and mouth. In case of contact with eyes, rinse eyes thoroughly with water.
--------------------------------------------------------------------------------------------------------
Stop use and ask a doctor if irritation or rash occurs. These may be signs of a serious condition.

KEEP OUT OF REACH OF CHILDREN

If swallowed, get medical help or contact a Poison Control Center right away.

Uses

Hand sanitizer to help reduce bacteria that potentially can cause disease.

Directions

• Place enough product on hands to cover all surfaces. Rub hands together until dry.
• Supervise children under 6 years of age when using this product to avoid swallowing.

Other information

• Store between 15-30℃ (59-86F)
• Avoid freezing and excessive heat above 40℃ (104F)